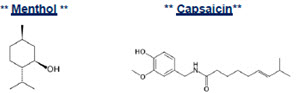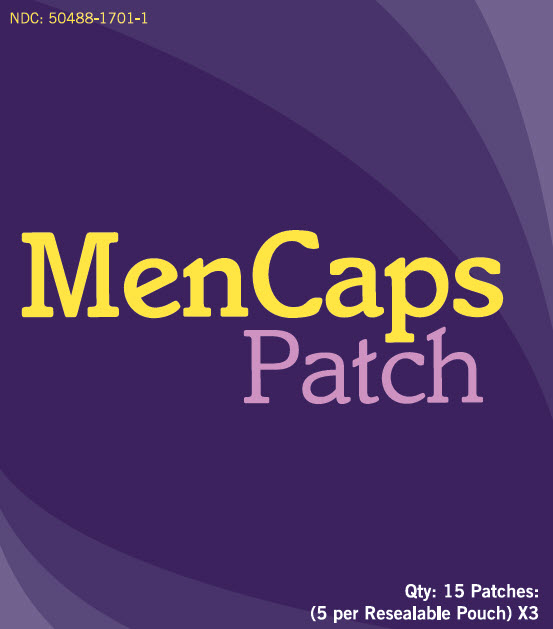 DRUG LABEL: MenCaps
NDC: 50488-1701 | Form: PATCH
Manufacturer: Alexso Inc
Category: otc | Type: HUMAN OTC DRUG LABEL
Date: 20190212

ACTIVE INGREDIENTS: CAPSAICIN 0.0225 g/1 1; MENTHOL, UNSPECIFIED FORM 4.5 g/1 1
INACTIVE INGREDIENTS: WATER; GLYCERIN; SODIUM POLYACRYLATE (8000 MW); POLYSORBATE 80; LEMON PEEL; ALOE VERA LEAF; EDETATE DISODIUM; DIAZOLIDINYL UREA; METHYLPARABEN; IODOPROPYNYL BUTYLCARBAMATE; PROPYLPARABEN

MenCaps Patch

Active ingredients:

Menthol 4.5%

Purpose

Topical Analgesic

Active ingredients:

Capsaicin 0.0225%

Purpose

Topical Anesthetic

Uses:

For temporary relief of minor aches & pains of muscles & joints associated with arthritis, simple backache, strains, bruises, and sprains.

Directions:

Adults and children 12 years and over: Apply 1 patch to the affected area of intact skin up to 3 times a day. Do not leave patch on for more than 8 hours at a time.

Instructions for Use:

- Clean and dry the affected area.
- Open pouch and remove one patch.
- Remove any protective film and apply directly to affected area of pain.
  Apply immediately after removal from the protective envelope.
- Wash hands with soap and water after handling the patches.
- Reseal pouch containing unused patches after each use. Do not store patch outside the sealed envelope.
- Discontinue use at least 1 hour before a bath or shower and do not use immediately after a bath or shower.
- Fold used patches so that the adhesive side sticks to itself and safely discard used patches or pieces of cut patches where children and pets cannot get to them.

Warnings:

- For external use only. Use only as directed or by a health professional.
- Do not use: On wounds, cuts, damaged or infected skin.
  - On eyes, mouth, genitals, or any other mucus membranes.
- Stop and consult your physician if pregnant or if pain worsens
- Allergy Alert: if you are allergic to any ingredients of this product or chili peppers contact a doctor before use.

Keep out of reach of children.

Consult physician for children under 12.

Other Ingredients:

Water, Glycerol, Sodium Polyacrylate, Polysorbate 80, Citrus Medica Limonum (Lemon) Peel Oil, Aloe Barbadensis Leaf (Aloe Vera Gel) Juice, EDTA Disodium salt, Diazolidinyl Urea, Methylparaben, Iodopropynyl Butylcarbamate, Propylparaben.

Questions or Comments

Call 888.495.6078

PACKAGE INSERT

Patient Information

(updated 6/2015)

Read the patient information sheet provided before you start using this medication and each time you get a refill. If you have any questions, please consult your doctor or pharmacist. Inform your doctor if your condition does not improve or if it worsens.

This information may not include all of the information needed to use MenCaps Patch® safely and effectively.

For Topical Use Only

What is MenCaps Patch®?

This is a topical patch consisting of the topical analgesic, menthol, and the topical analgesic, capsaicin extract.

What is MenCaps Patch® used for?

The patch is applied to the skin assisting patients in the management of mild to moderate acute or moderate aches or pain of muscles and joints associated with arthritis, backache, strains and sprains. The diagnosis of acute or chronic topical pain can be made relatively simply by the diagnostic practitioner, however uncovering the underlying pathology manifesting as pain and discomfort is often more difficult.

The combination of capsaicin and menthol is a highly effective combination of working synergistically to ease the discomfort while the root cause is being managed and treated by your healthcare team.

DO NOT USE:

- If you are allergic to any of the ingredients in this product
- On wounds or damaged skin
- With a heating pad
- Concurrently with any other external pain-relieving products

What are the possible side effects with MenCaps Patch®

- Common (≥10%): itching, redness or flaking of the skin following application (note: the majority of patients experience no significant adverse events following patch application).
- NOTE: serious side effects are, in general, related to accidental toxicity of medication by applying considerably more than directed by your doctor or pharmacist
- Tell your healthcare provider about all the medicines you take. This includes prescription and nonprescription medicines, vitamins, and herbal supplements

WARNINGS:

1. Do not use:
2. On wounds, cuts, damaged or infected skin
3. On eyes, mouth, genitals, or other mucous membranes
2. Consult physician for children under 12 years of age
3. Stop and consult your prescriber if pain worsens
4. DISCONTINUE USE AT LEAST 1 HOURS BEFORE A BATH OR SHOWER AND DO NOT USE IMMEDIATELY AFTER A BATH OR SHOWER

Call your healthcare provider right away if you get any of the following warning signs or any other unusual symptoms that concern you:

- Shortness of breath
- Swelling or numbness of the tongue or throat
- Severe headache or vomiting
- Dizziness or faintness
- Changes in vision or speech

This is not a complete list of the possible side effects. For more information, talk with your doctor or pharmacist. You may report side effects to FDA at 1-800-FDA-1088 or www.fda.gov/medwatch.

DIRECTIONS FOR USE:

Adults and children 12 years and over: Apply 1 patch to the affected area of intact skin up to 3 times a day. MenCaps Patch® should not be left on for more than 8 hours at a time.

1. Clean and dry the affected area.
2. Open pouch and remove one patch.
3. Remove any protective film and apply directly to the painful area. Apply immediately after opening.
4. Wash hands with soap and water after handling the patches.
5. Reseal pouch containing unused patches after each use. Do not store patch outside the sealed envelope.
6. Fold used patches so that the adhesive side sticks to itself. Next, safely discard the used patches or pieces of cut patches where children and pets cannot get to them.

Children under 12 years of age:

- Consult a doctor.

General information about the safe and effective use
MenCaps Patch®

Medicines are sometimes prescribed for purposes other than those listed in a patient information leaflet. Do not use this product for another indication. Your doctor has prescribed this drug for you and you alone. Do not give this drug to anyone else, even if they have the same condition.

How should I store MenCaps Patch®

Store product at room temperature at 68°F to 77°F (20°C to 25°C). Keep away from heat and sunlight. Protect from excessive moisture. Discard product after expiration date posted on the product label.

DO NOT use the product after the expiration date printed on the box.

KEEP OUT OF REACH OF CHILDREN

This leaflet provides the most important information about MenCaps Patch®. If you would like more information, talk with your healthcare provider or pharmacist. There is additional information in the following sections intended for healthcare professionals.

What are the active ingredients in MenCaps Patch®?

The patch consists of 4.5% menthol and 0.0225% capsaicin.

INACTIVE INGREDIENTS:

Water Aloe Barbadesis Leaf (Aloe Vera Gel)
Glycerol EDTA Disodium salt
Sodium Polyacrylate Diazolidinyl Urea
Polysorbate 80 Methylparaben
Propylparaben Citrus Medica Limonum
Iodopropynyl Butylcarbamate (Lemon) Peel Oil

PRESCRIBER INFORMATION

MenCaps Patch® (Menthol 4.5% / Capsaicin 0.0225% Topical Patch)

DESCRIPTION:

MenCaps Patch® is an OTC topical patch containing 15 articulated MenCaps patches (5 per re-sealable pouch x 3 pouches). Capsaicin is present in a 0.0225% concentration (w/w). It is chemically designated as (E)-N-[(4-Hydroxy-3-methoxyphenyl) methyl]-8- methylnon-6-enamide and has an empirical formula of C18H27NO3. The molecular weight of capsaicin is 305.41 g/mol. Menthol is present in a 4.5% concentration (w/w). The chemical name is (1R,2S,5R)-2- isopropyl-5-methylcyclohexanol. The empirical formula for menthol is C10H20O with a molecular weight of 156.27 g/mol.

The structural formulas are:

Box Label

CLINICAL PHARMACOLOGY:

Capsaicin is an active component of chili peppers known clinically as a rubefacient. It acts as a counter-irritant by producing heat when in contact with human tissue. Mechanistically, capsaicin exerts its analgesic and anti-inflammatory effects by mimicking a burning sensation – whereby overwhelming the nerves by calcium influx, thereby rendering the nerves unable to signal a pain response for an extended period of time. With repeated exposure, the neurons become depleted of neurotransmitters –specifically substance P - leading to a reduction in the sensation of pain and the blockade of neurogenic inflammation. This process is reversed when the capsaicin is discontinued.

Menthol has local anesthetic and counterirritant qualities, and it also acts as a weak kappa (κ) opioid receptor agonist. Menthol acts to chemically trigger the cold-sensitive TRPM-8 receptors in the skin - responsible for the well-known cooling sensation it stimulates when applied directly to the skin. Menthol's analgesic properties are not fully understood, however they are mediated through a selective activation of κ-opioid receptors. Menthol also blocks voltage-sensitive sodium channels, reducing neural activity that may stimulate muscle tissue.

INDICATIONS AND USAGE:

MenCaps Patch® is a formulation used to assist patients for the temporary relief of minor aches & pains of muscles & joints associated with arthritis, simple backache, strains, bruises, and sprains. Peripheral neuropathies such as diabetic neuropathy or post herpetic neuralgia, may also be symptomatically improved using this patch if recommended by the healthcare team.

Other uses may be considered if deemed clinically relevant.

CONTRAINDICATIONS:

Known hypersensitivity to menthol, capsaicin, or any of the inactive ingredients listed above.

WARNINGS:

1. Do not use on wounds, cuts, damaged or infected skin
2. Do not use on eyes, mouth, genitals, or any other mucous membranes
3. Keep out of reach of children

PRECAUTIONS:

Because of the possibility of sedation, patients should be cautioned regarding the operation of serious machinery or automobiles, and activities made hazardous by decreased alertness.

DRUG INTERACTIONS:

No Drug interactions have been assessed with MenCaps Patch®

CARCINOGENESIS, MUTAGENESIS, IMPAIRMENT OF FERTILITY:

Nonclinical toxicity studies to determine the potential of this topical preparation to cause carcinogenicity or mutagenicity have not been performed. The effect of the product on fertility has not been evaluated in animals.

PREGNANCY:

The safety of MenCaps Patch® has not been established during pregnancy. There are no well-controlled studies in pregnant women.

PEDIATRIC / GERIATRIC USE:

Safety and effectiveness in pediatric and geriatric patients have not been established.

NURSING MOTHERS:

The effect of MenCAps Patch® on the nursing infant has not been evaluated.

ADVERSE REACTIONS:

The most common adverse reactions are application site reactions, including dermatitis, itching or scaling. These tend to be dose-limiting and diminish with time.

Serious adverse experiences following the administration of MenCaps Patch® are similar in nature to those observed in other amide anesthetic-containing agents. These adverse experiences are, in general, dose-related and may result from high plasma levels caused by excessive dosage, rapid absorption, or may result from hypersensitivity, idiosyncrasy, or a diminished tolerance on the part of the patient. Serious adverse experiences are generally systemic in nature.

OVERDOSAGE:

There have been no reports of over-dosage with MenCaps Patch®. Signs of overdosage would include vomiting, drowsiness, coma, respiratory depression, and seizures. In the case of an overdosage, discontinue the product immediately, treat the patient symptomatically, and institute supportive measures.

STORAGE:

Store at room temperature at 68°F to 77°F (20°C to 25°C). Keep away from heat or sunlight. Protect from excessive moisture. The product can be considered safe and effective to use when maintained under these recommended conditions within the posted expiration date.

HOW SUPPLIED:

MenCaps Patch® is supplied in the following dosage form:

- 15 Articulated Patches [(5 per Re-sealable Pouch) x 3]

Manufactured for : Alexso Inc
2317 Cotner Ave • Los Angeles, CA 90064
www.alexso.com • 888.495.6078

NDC: 50488-1701-1 Size: 15 Patches

Package/Label Principal Display Panel

NDC 50488-1701-1

MenCaps

Patch

Qty: 15 Patches

(5 per Resealable Pouch) x 3

Box Label